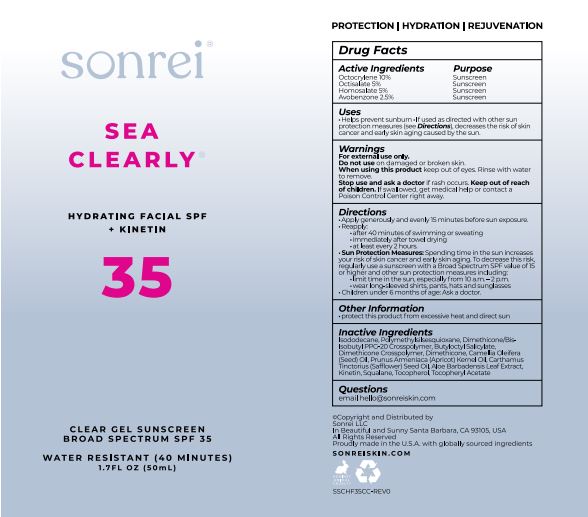 DRUG LABEL: Sea Clearly Hydrating Facial SPF 35 Kinetin
NDC: 62742-4237 | Form: CREAM
Manufacturer: Allure Labs
Category: otc | Type: HUMAN OTC DRUG LABEL
Date: 20231205

ACTIVE INGREDIENTS: OCTISALATE 5 g/100 g; OCTOCRYLENE 10 g/100 g; HOMOSALATE 5 g/100 g; AVOBENZONE 2.5 g/100 g
INACTIVE INGREDIENTS: DIMETHICONE CROSSPOLYMER (450000 MPA.S AT 12% IN CYCLOPENTASILOXANE); POLYMETHYLSILSESQUIOXANE/TRIMETHYLSILOXYSILICATE; KINETIN; DIMETHICONE/BIS-ISOBUTYL PPG-20 CROSSPOLYMER; TOCOPHEROL; CAMELLIA OIL; APRICOT KERNEL OIL; ISODODECANE; BUTYLOCTYL SALICYLATE; DIMETHICONE; SAFFLOWER OIL; SQUALANE; .ALPHA.-TOCOPHEROL ACETATE; ALOE VERA LEAF

Drug Facts

Active ingredient,

Octocrylene – 10 %

Octisalate – 5%

Homosalate – 5%

Avobenzone – 2.5 %

Purpose: Sunscreen

INDICATIONS AND USAGE

Uses. Helps prevent sunburn.

If used as directed with other sun protection measures (see Direction), decreases the risk of skin cancer and early skin aging caused by the sun.

Warnings

For external use only.

Do not use on damaged or broken skin.

When using this product keep out of eye.Rinse with water to remove.

Stop use and ask doctor if skin rash occurs.

Keep out of reach of children, If product is swallowed, get medical help or contact a poison control center right away.

Directions.

Apply generously and evenly 15 minutes before sun exposure.

Reapply: after 40 minutes of swimming or sweating.

Immediately after towel drying. At least every 2 hours.

Sun Protection Measures: Spending time the sun increases your risk of skin cancer and early skin aging. To decrease this risk, regularly use of sunscreen with a broad spectrum SPF value of 15 or higher and other sun protection measures including: limit time in the sun, especially from 10 a.m. – 2 p.m. wear long-sleeved shirts, pants, hats and sunglasses. Children under 6 months of age: Ask a doctor.

Other information.

Protect this product from excessive heat and direct sun.

Inactive ingredient:

Isododecane, Polymethylsilsesquioxane, Dimethicone/Bis-Isobutyl PPG-20 Crosspolymer, Butyloctyl Salicylate, Dimethicone Crosspolymer, Dimethicone,Camellia Oleifera (Seed) Oil,Prunus Armeniaca (Apricot) Kernel Oil, Carthamus Tinctorius (Safflower) Seed Oil, Aloe Barbandensis Leaf Extract, Kinetin, Squalane,Tocopherol, Tocopheryl Acetate.